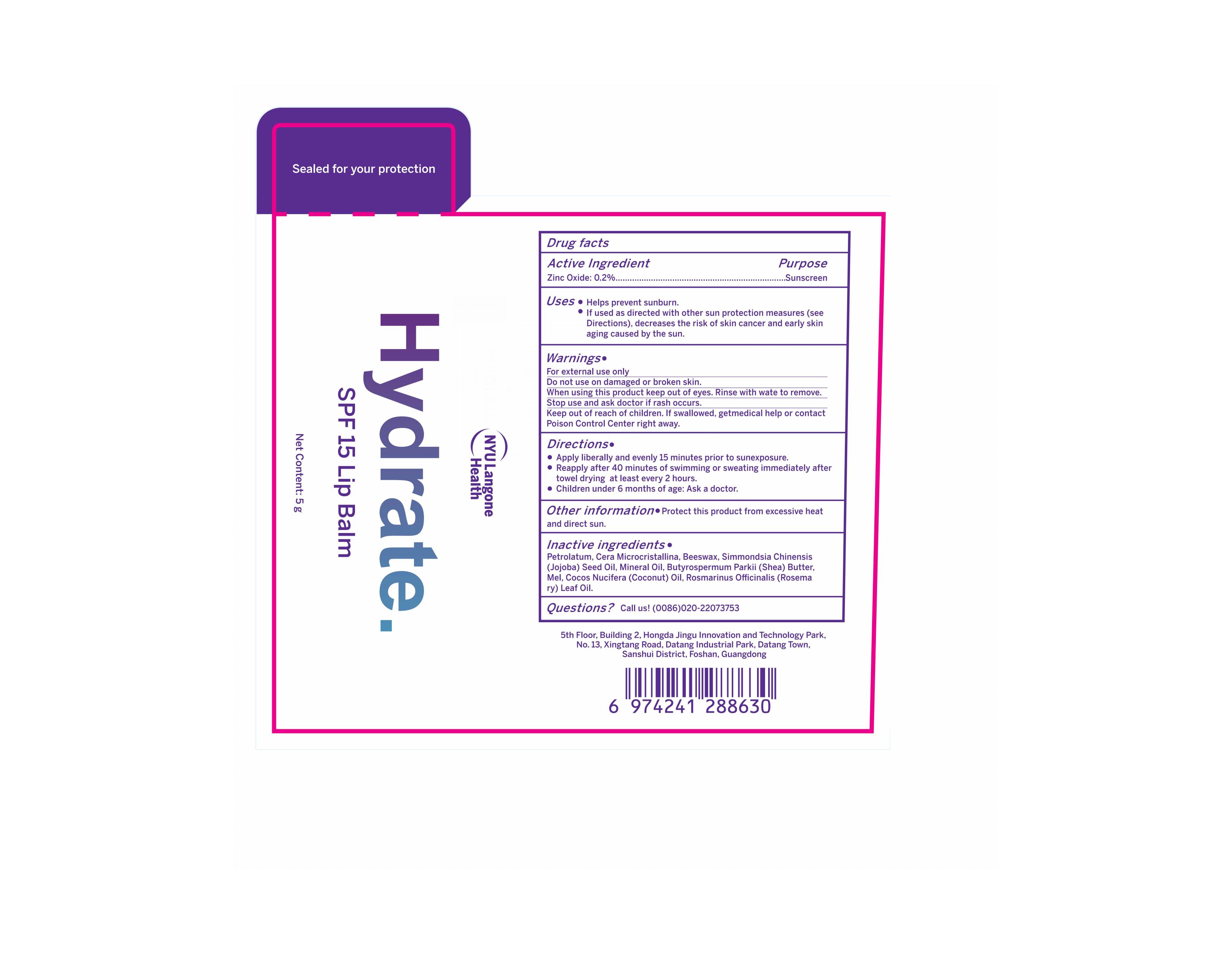 DRUG LABEL: NYU Langone Health Lip Balm
NDC: 83566-558 | Form: LIPSTICK
Manufacturer: Guangdong Aimu Biological Technology Co., Ltd
Category: otc | Type: HUMAN OTC DRUG LABEL
Date: 20250626

ACTIVE INGREDIENTS: ZINC OXIDE 0.2 g/100 g
INACTIVE INGREDIENTS: MINERAL OIL; SIMMONDSIA CHINENSIS (JOJOBA) SEED OIL; BEESWAX; COCOS NUCIFERA (COCONUT) OIL; ROSMARINUS OFFICINALIS (ROSEMARY) LEAF OIL; PETROLATUM

NYU Langone Health Lip Balm

Active ingredients

Zinc Oxide 0.2%

Purpose

Lip sun protection

Uses

Apply liberally and evenly 15 minutes prior to sunexposure.
Reapply after 40 minutes of swimming or sweating immediately after towel drying "at least every 2 hours.

Warnings

For external use only.

Stop use and ask a doctor if

rash occurs.

Do not use

on damaged or broken skin.

When using this product

keep out of eyes. Rinse with water to remove.

Keep out of reach of children.

If swallowed, get medical help or contact a Poison Control Center right away.

Dosage

Squeeze out an appropriate amount of Sunscreen lip balm and spread evenly on your lips.

Inactive ingredients

PETROLATUM：69%
CERA MICROCRISTALLINA：13%
BEESWAX：5%
SIMMONDSIA CHINENSIS (JOJOBA) SEED OIL：5%
MINERAL OIL：4.4%
BUTYROSPERMUM PARKII(SHEA) BUTTER：2%
MEL：1%
COCOS NUCIFERA (COCONUT) OIL：0.2%
ROSMARINUS OFFICINALIS (ROSEMARY) LEAF OIL：0.2%